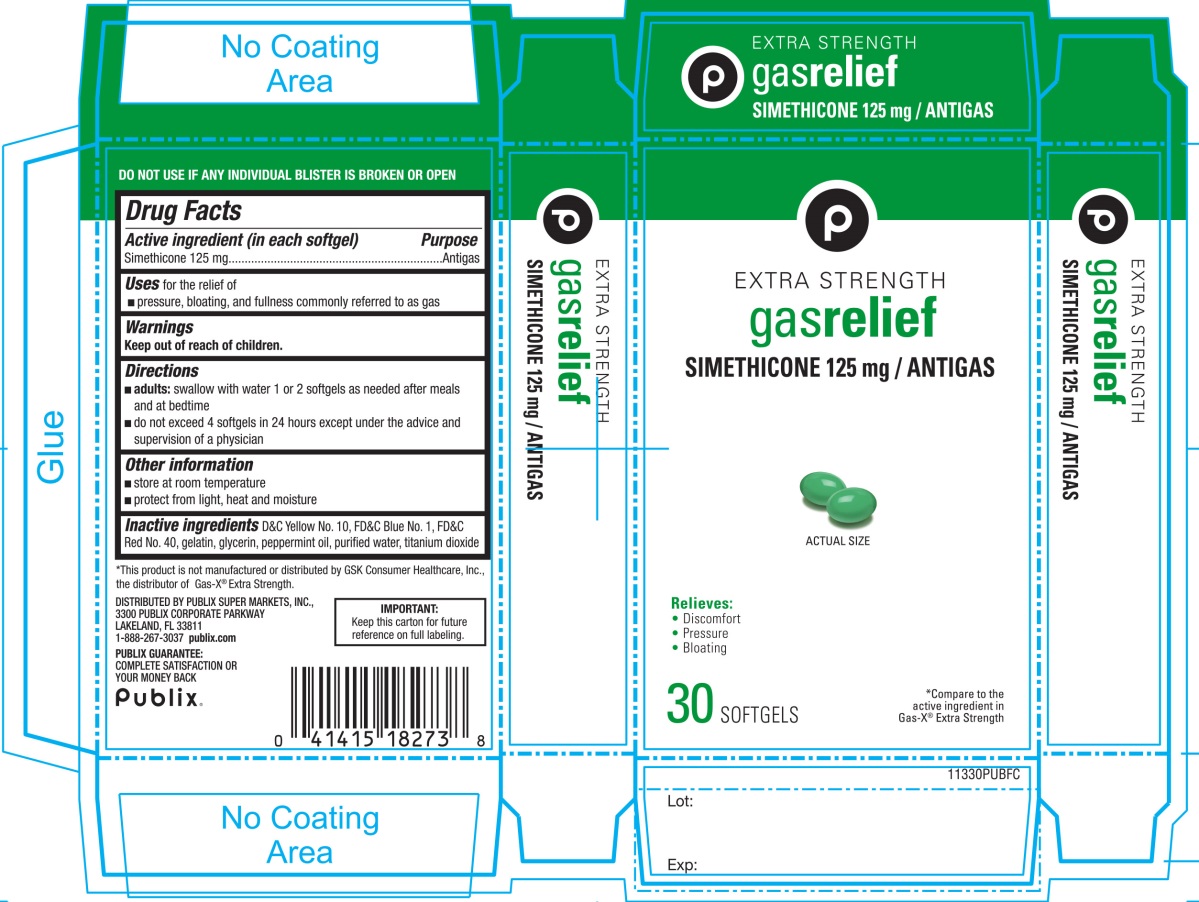 DRUG LABEL: PUBLIX

NDC: 41415-113 | Form: CAPSULE, LIQUID FILLED
Manufacturer: PUBLIX SUPER MARKETS, INC
Category: otc | Type: HUMAN OTC DRUG LABEL
Date: 20251028

ACTIVE INGREDIENTS: DIMETHICONE, UNSPECIFIED 125 mg/1 1
INACTIVE INGREDIENTS: D&C YELLOW NO. 10; FD&C BLUE NO. 1; FD&C RED NO. 40; GELATIN, UNSPECIFIED; GLYCERIN; PEPPERMINT OIL; WATER; TITANIUM DIOXIDE

Publix Extra Strength Gas Relief 30 Softgels Drug Facts

Active ingredient (in each softgel)

Simethicone 125 mg

Purpose

Antigas

Uses

for relief of:

- pressure, bloating and fullness commonly referred to as gas

Directions

- adults:swallow with water 1 or 2 softgels as needed after meals and at bedtime.
- do not exceed 4 softgels in 24 hours except under the advice and supervision of a physician.

Other information

- store at room temperature
- protect from light, heat and moisture.

Inactive ingredients

D&C yellow No. 10, FD&C blue No. 1, FD&C red No. 40, gelatin, glycerin, peppermint oil, purified water, titanium dioxide.

Questions or comments?

1-866-467-2748

Principal Display Panel

NDC 41415-113-30

*Compare to the active ingredient Gas-X® Extra Strength

Extra Strength

Gas Relief

SIMETHICONE 125 MG/ ANTI-GAS

Relieves:

- Discomfort
- Pressure
- Bloating

30 SOFTGELS

IMPORTANT:Keep this carton for future reference on full labeling.

DISTRIBUTED BY: PUBLIX SUPER MARKETS, INC.,

3300 PUBLIX CORPORATE PARKWAY

LAKELAND, FL 33811

1-888-267-3037 publix.com

PUBLIX GUARANTEE:

COMPLETE SATISFACTION OR YOUR MONEY BACK

*This product is not manufactured or distributed by GSK Consumer Healthcare, Inc., the distributor of Gas-X®Extra Strength.

DO NOT USE IF ANY INDIVIDUAL BLISTERS UNIT IS BROKEN OR OPEN.